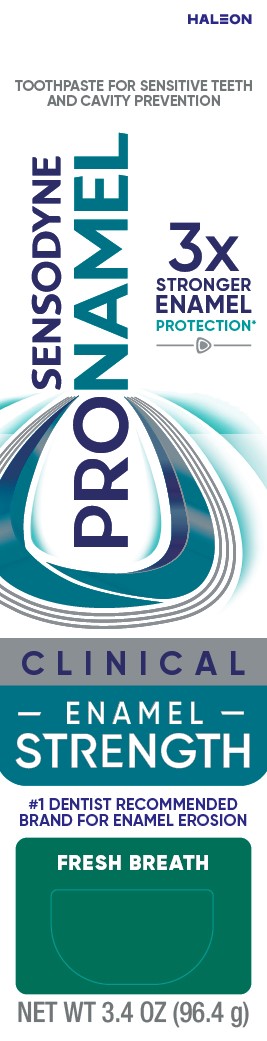 DRUG LABEL: Sensodyne

NDC: 0135-7753 | Form: PASTE, DENTIFRICE
Manufacturer: Haleon US Holdings LLC
Category: otc | Type: HUMAN OTC DRUG LABEL
Date: 20251201

ACTIVE INGREDIENTS: POTASSIUM NITRATE 50 mg/1 g; SODIUM FLUORIDE 1.5 mg/1 g
INACTIVE INGREDIENTS: WATER; SORBITOL; HYDRATED SILICA; GLYCERIN; POLYETHYLENE GLYCOL 400; SODIUM LACTATE; COCAMIDOPROPYL BETAINE; XANTHAN GUM; SILICON DIOXIDE; TITANIUM DIOXIDE; SACCHARIN SODIUM; METHYL VINYL ETHER AND MALEIC ACID COPOLYMER (1750000 WAMW); SODIUM HYDROXIDE

Drug Facts

Active ingredients

Potassium nitrate 5%

Sodium fluoride 0.25% (0.15% w/v fluoride ion)

Purposes

Antihypersensitivity

Anticavity

Uses

- builds increasing protection against painful sensitivity of the teeth to cold, heat, acids, sweets, or contact.
- aids in the prevention of dental cavities.

Warnings

Stop use and ask a dentist if

- the problem persists or worsens. Sensitive teeth may indicate a serious problem that may need prompt care by a dentist.
- pain/sensitivity still persists after 4 weeks of use.

Keep out of reach of children.

If more than used for brushing is accidentally swallowed, get medical help or contact a Poison Control Center right away.

Directions

- adults and children 12 years of age and older:
  - apply at least a 1-inch strip of the product onto a soft bristle toothbrush.
  - brush teeth thoroughly for at least 1 minute twice a day (morning and evening) or as recommended by a dentist or doctor. Make sure to brush all sensitive areas of the teeth. Minimize swallowing.
- children under 12 years of age:Consult a dentist or doctor.

Other information

- do not store above 25°C (77°F)

Inactive ingredients

water, sorbitol, hydrated silica, glycerin, PEG-8, sodium lactate, flavor, cocamidopropyl betaine, xanthan gum, silica, titanium dioxide, sodium saccharin, PVM/MA copolymer, sodium hydroxide

Questions or comments?

1-866-844-2797

Additional Information

ALWAYS FOLOW THE LABEL

SENSODYNE PRONAMEL CLINICAL ENAMEL STRENGTH

CLINICALLY PROVEN ENAMEL STRENGTHENING

REPAIRS

66%of enamel microdamage in the most vulnerable areas of your teeth^

24/7 PROTECTION

against early stage cavities, sensitivity and future enamel damage**

To help protect teeth for life**

LEAVES YOUR MOUTH

feeling clean and fresh

FRESH MINT

*Vs. your mouth’s natural defenses.

**With twice daily brushing.

^Acid weakened enamel. On average as shown in 7 day lab test.

Principal Display Panel

TOOTHPASTE FOR SENSITIVE TEETH AND CAVITY PROTECTION

SENSODYNE PRONAMEL

3x STRONGER ENAMEL PROTECTION*

CLINICAL ENAMEL STRENGTH

#1 DENTIST RECOMMENDED BRAND FOR ENAMEL EROSION

FRESH BREATH

NET WT 3.4 OZ (96.4 g)